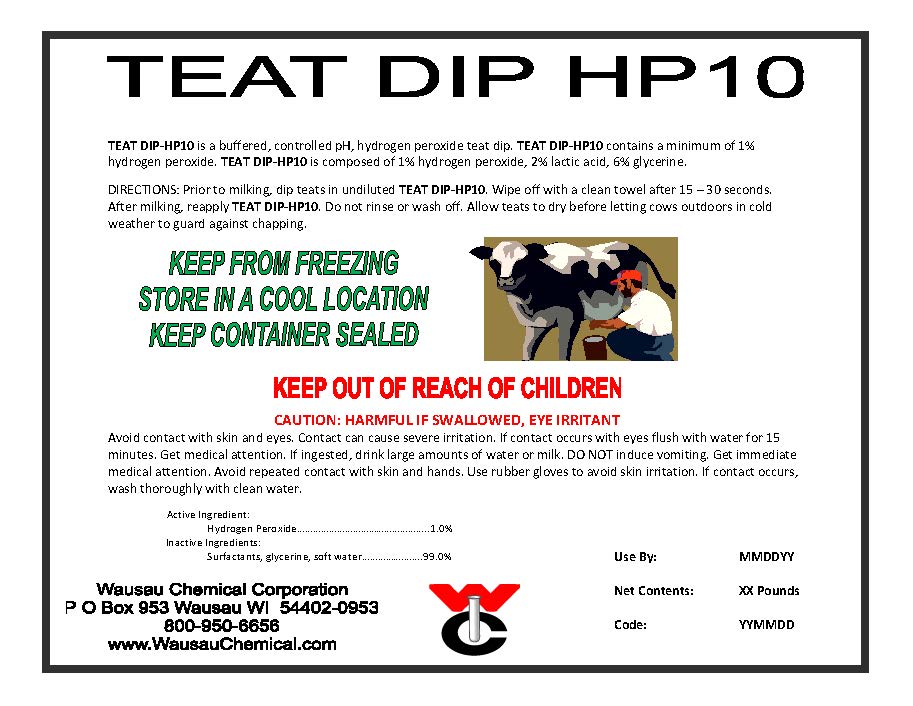 DRUG LABEL: Teat Dip HP 10
NDC: 64892-007 | Form: SOLUTION
Manufacturer: Wausau Chemical
Category: animal | Type: OTC ANIMAL DRUG LABEL
Date: 20120529

ACTIVE INGREDIENTS: Hydrogen Peroxide 1 L/100 L

GENERAL PRECAUTIONS

FOR COMMERCIAL USE ONLY

KEEP OUT OF REACH OF CHILDREN

NOT FOR HUMAN USE

CAUTION

Harmful if swallowed, eye irritant.

FIRST AID:

Avoid contact with skin and eyes. Contact can cause severe irritation. If contact occurs with eyes flush with water for 15 minutes. Get medical attention. If ingested, drink large amounts of water or milk. DO NOT induce vomiting. Get immediate medical attention. Avoid repeated contact with skin and hands. Use rubber gloves to avoid skin irritation. If contact occurs, wash thoroughly with clean water.

EMERGENCY : CHEMTREC 800-424-9300

Directions:
Prior to milking, dip teats in undiluted TEAT DIP HP 10. Wipe off with a clean towel after 15-30 seconds. After milking reapply TEAT DIP HP 10. Do not rinse or wash off. Allow teats to dry before letting cows outdoors in cold weather to guard against chapping.

PRINCIPAL DISPLAY PANEL/ REPRESENTATIVE LABEL

Teat Dip HP 10

Non-Iodine Teat Dip

An Aid in Reducing the Spread of Organisms

Which May Cause Mastitis

ACTIVE INGREDIENTS:

Hydrogen Peroxide...............................1.0%

INACTIVE INGREDIENTS...................99.0%

Wausau Chemical Corporation

2001 North River Drive

Wausau, WI 54403-0953 U.S.A.